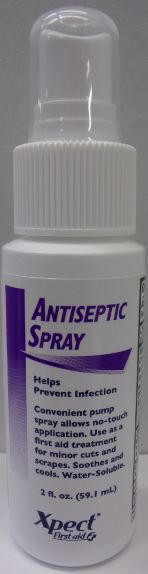 DRUG LABEL: Xpect Antiseptic
NDC: 42961-227 | Form: SPRAY
Manufacturer: Cintas Corporation
Category: otc | Type: HUMAN OTC DRUG LABEL
Date: 20250922

ACTIVE INGREDIENTS: BENZALKONIUM CHLORIDE 0.13 mg/1 mL
INACTIVE INGREDIENTS: ALCOHOL; WATER

Xpect Antiseptic Spray

Active ingredients

Benzalkonium chloride 0.13%

Purpose

first aid antiseptic

Uses

first aid to help prevent infection in minor cuts, scrapes and burns

Warnings

For external use only

Do not use

- in the eyes or apply over large areas of the body
- longer than 1 week unless directed by a doctor

Ask a doctor before use if you have

- deep or puncture wounds
- animal bites
- serious burns

Stop use and ask a doctor if

- condition persists or gets worse

Keep out of reach of children. If swallowed, get medical help or contact a Poison Control Center right away.

Directions

- clean the affected area
- spray a small amount 1 to 3 times daily
- may be covered with a sterile bandage.
- if bandaged, let dry first.

Other information

- shake well
- store at room temperature

Inactive ingredients

alcohol, water

Questions?

1-877-973-2811 M-F 8am-5pm

Principal Display Panel

ANTISEPTIC SPRAY

Helps Prevent Infection

Convenient pump spray allows no-touch

application. Use as a first aid treatment

for minor cuts and scrapes. Soothes and

cools. Water-Soluble.

2 fl. oz. (59.1 mL)

Xpect® First aid